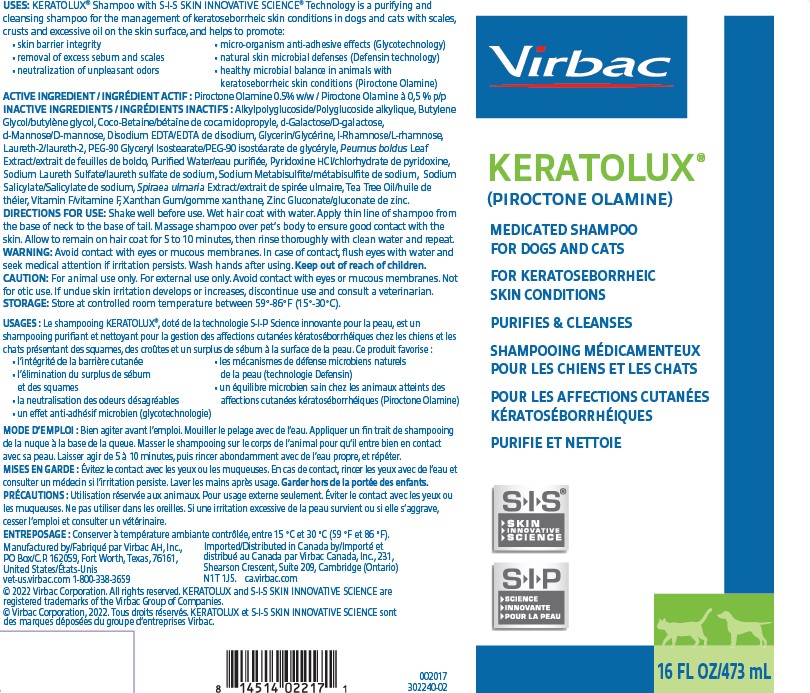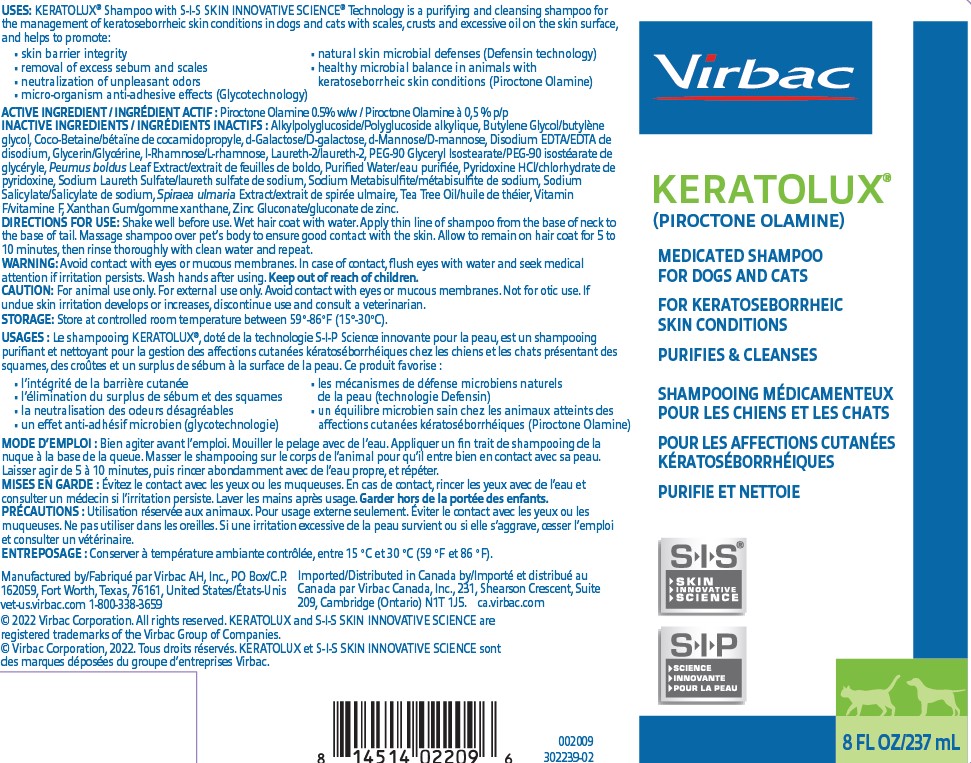 DRUG LABEL: Keratolux
NDC: 51311-072 | Form: SHAMPOO
Manufacturer: Virbac AH, Inc.
Category: animal | Type: OTC ANIMAL DRUG LABEL
Date: 20240227

ACTIVE INGREDIENTS: PIROCTONE OLAMINE 5 mg/1 mL

KERATOLUX® (piroctone olamine) medicated shampoo for dogs and cats

MEDICATED SHAMPOO FOR DOGS AND CATS FOR KERATOSEBORRHEIC SKIN CONDITIONS PURIFIES & CLEANSESSHAMPOOING MÉDICAMENTEUX POUR LES CHIENS ET LES CHATS POUR LES AFFECTIONS CUTANÉES KÉRATOSÉBORRHÉIQUES PURIFIE ET NETTOIE

USES:

KERATOLUX® Shampoo with S-I-S SKIN INNOVATIVE SCIENCE® Technology is a purifying and cleansing shampoo for the management of keratoseborrheic skin conditions in dogs and cats with scales, crusts and excessive oil on the skin surface, and helps to promote:

• skin barrier integrity
• removal of excess sebum and scales
• neutralization of unpleasant odors
• micro-organism anti-adhesive effects (Glycotechnology)
• natural skin microbial defenses (Defensin technology)
• healthy microbial balance in animals with keratoseborrheic skin conditions (Piroctone Olamine)

USAGES:

Le shampooing KERATOLUX®, doté de la technologie S-I-P Science innovante pour la peau, est un shampooing purifiant et nettoyant pour la gestion des affections cutanées kératoséborrhéiques chez les chiens et les chats présentant des squames, des croûtes et un surplus de sébum à la surface de la peau. Ce produit favorise :

• l’intégrité de la barrière cutanée
• l’élimination du surplus de sébum et des squames
• la neutralisation des odeurs désagréables
• un effet anti-adhésif microbien (glycotechnologie)
• les mécanismes de défense microbiens naturels de la peau (technologie Defensin)
• un équilibre microbien sain chez les animaux atteints des

ACTIVE INGREDIENT / INGRÉDIENT ACTIF:

Piroctone Olamine 0.5% w/w

Piroctone Olamine à 0,5 % p/p

INACTIVE INGREDIENTS / INGRÉDIENTS INACTIFS:

Alkylpolyglucoside/Polyglucoside alkylique, Butylene Glycol/butylène glycol, Coco-Betaine/bétaïne de cocamidopropyle, d-Galactose/D-galactose, d-Mannose/D-mannose, Disodium EDTA/EDTA de disodium, Glycerin/Glycérine, l-Rhamnose/L-rhamnose, Laureth-2/laureth-2, PEG-90 Glyceryl Isostearate/PEG-90 isostéarate de glycéryle, Peumus boldus Leaf Extract/extrait de feuilles de boldo, Purified Water/eau purifiée, Pyridoxine HCl/chlorhydrate de pyridoxine, Sodium Laureth Sulfate/laureth sulfate de sodium, Sodium Metabisulfite/métabisulfite de sodium, Sodium Salicylate/Salicylate de sodium, Spiraea ulmaria Extract/extrait de spirée ulmaire, Tea Tree Oil/huile de théier, Vitamin F/vitamine F, Xanthan Gum/gomme xanthane, Zinc Gluconate/gluconate de zinc.

DIRECTIONS FOR USE / MODE D’EMPLOI:

Shake well before use. Wet hair coat with water. Apply thin line of shampoo from the base of neck to the base of tail. Massage shampoo over pet’s body to ensure good contact with the skin. Allow to remain on hair coat for 5 to 10 minutes, then rinse thoroughly with clean water and repeat.

Bien agiter avant l’emploi. Mouiller le pelage avec de l’eau. Appliquer un fin trait de shampooing de la nuque à la base de la queue. Masser le shampooing sur le corps de l’animal pour qu’il entre bien en contact avec sa peau. Laisser agir de 5 à 10 minutes, puis rincer abondamment avec de l’eau propre, et répéter.

WARNING / MISES EN GARDE:

Avoid contact with eyes or mucous membranes. In case of contact, flush eyes with water and seek medical attention if irritation persists. Wash hands after using. Keep out of reach of children.

Évitez le contact avec les yeux ou les muqueuses. En cas de contact, rincer les yeux avec de l’eau et consulter un médecin si l’irritation persiste. Laver les mains après usage. Garder hors de la portée des enfants.

CAUTION / PRÉCAUTIONS:

For animal use only. For external use only. Avoid contact with eyes or mucous membranes. Not for otic use. If undue skin irritation develops or increases, discontinue use and consult a veterinarian.

Utilisation réservée aux animaux. Pour usage externe seulement. Éviter le contact avec les yeux ou les muqueuses. Ne pas utiliser dans les oreilles. Si une irritation excessive de la peau survient ou si elle s’aggrave, cesser l’emploiet consulter un vétérinaire.

STORAGE / ENTREPOSAGE:

Store at controlled room temperature between 59°-86°F (15°-30°C).

Conserver à température ambiante contrôlée, entre 15 °C et 30 °C (59 °F et 86 °F).

QUESTIONS?

Manufactured by/Fabriqué par Virbac AH, Inc.,

PO Box/C.P. 162059, Fort Worth, Texas, 76161, United States/États-Unis

vet-us.virbac.com 1-800-338-3659

Imported/Distributed in Canada by/Importé et distribué au

Canada par Virbac Canada, Inc., 231, Shearson Crescent, Suite

209, Cambridge (Ontario) N1T 1J5. ca.virbac.com

© 2022 Virbac Corporation. All rights reserved. KERATOLUX and S-I-S SKIN INNOVATIVE SCIENCE are registered trademarks of the Virbac Group of Companies.
© Virbac Corporation, 2022. Tous droits réservés. KERATOLUX et S-I-S SKIN INNOVATIVE SCIENCE sont des marques déposées du groupe d’entreprises Virbac.

302239-02 and 302240-02